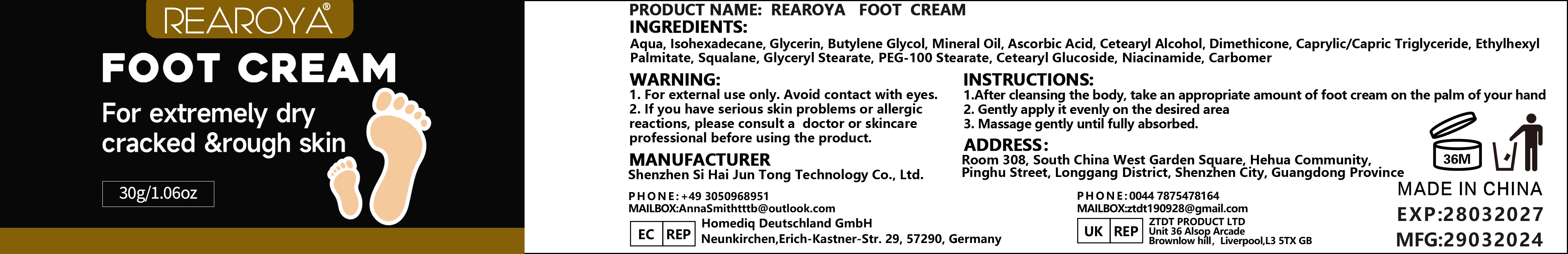 DRUG LABEL: REAROYAFOOTCREAM
NDC: 84350-017 | Form: CREAM
Manufacturer: Shenzhen Sihai Juntong Technology Co., Ltd
Category: otc | Type: HUMAN OTC DRUG LABEL
Date: 20240817

ACTIVE INGREDIENTS: SQUALANE 1 g/100 mg
INACTIVE INGREDIENTS: WATER

ACTIVE INGREDIENT

Niacinamide 5%

INACTIVE INGREDIENT

Water 5%

PURPOSE

Moisturizing

Warining

WARNING:1. For external use only. Avoid contact with eyes.2. lf you have serious skin problems or allergicreactions, please consult a doctor or skincareprofessional before using the product.

Do not use

if you have allergic reactions, stop to use

when using this product

1.After cleansing the body, take an appropriate amount of foot cream on the palm of your hand2. Gently apply it evenly on the desired area3. Massage gently until fully absorbed.

Keep out of reach of children

INDICATIONS AND USAGE

INSTRUCTIONS:1.After cleansing the body, take an appropriate amount of foot cream on the palm of your hand2. Gently apply it evenly on the desired area3. Massage gently until fully absorbed.

Dosage and administration

appropriate amount

PACKAGE LABEL

30g NDC84350-017-01